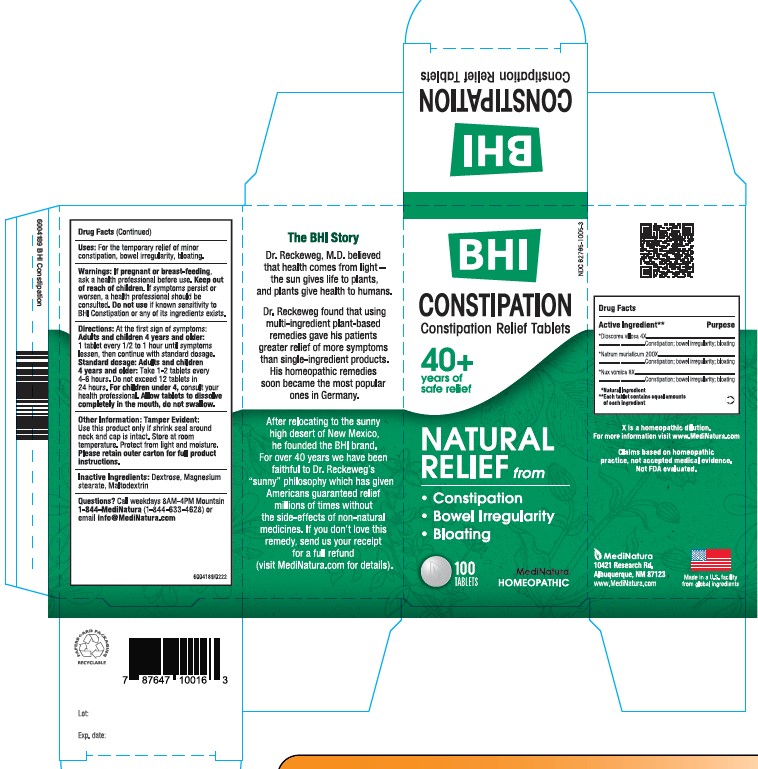 DRUG LABEL: BHI Constipation
NDC: 62795-1005 | Form: TABLET
Manufacturer: MediNatura Inc
Category: homeopathic | Type: HUMAN OTC DRUG LABEL
Date: 20220707

ACTIVE INGREDIENTS: DIOSCOREA VILLOSA TUBER 4 [hp_X]/1 1; SODIUM CHLORIDE 200 [hp_X]/1 1; STRYCHNOS NUX-VOMICA SEED 8 [hp_X]/1 1
INACTIVE INGREDIENTS: MAGNESIUM STEARATE; DEXTROSE; MALTODEXTRIN

BHI Constipation Tablet

ACTIVE INGREDIENTS

Each tablet contains: *Dioscorea villosa 4X, Natrum muriaticum 200X, *Nux vomica 8X 100 mg each.

*Natural Ingredients

INACTIVE INGREDIENTS

Inactive Ingredients:Dextrose, Magnesium Stearate, Maltodextrin
.

PURPOSE

Constipation Relief Tablets

Relieves:

• Constipation

• Bowel Irregularity

• Bloating

USES

For the temporary relief of minor constipation, bowel irregularity, bloating

DIRECTIONS

At first sign of symptoms:

Adults and children 4 years and older: 1 tablet every 1/2 to 1 hour until symptoms lessen, then continue with standard dosage.

Standard dosage: Adults and children 4 years and older: Take1-2 tablets every 4 to 6 hours. Do not exceed 12 tablets in 24 hours.

For children under 4, consult your health professional.

Allow tablets to dissolve completely in the mouth, do not swallow.

WARNINGS

If pregnant or breast-feeding, ask a health professional before use.

Keep out of reach of children. If symptoms persist or worsen, a health professional should be consulted.

Do not use if known sensitivity to BHI Constipation or any of its ingredients exists.

KEEP OUT OF REACH OF CHILDREN

PACKAGE LABEL

Add image transcription here...